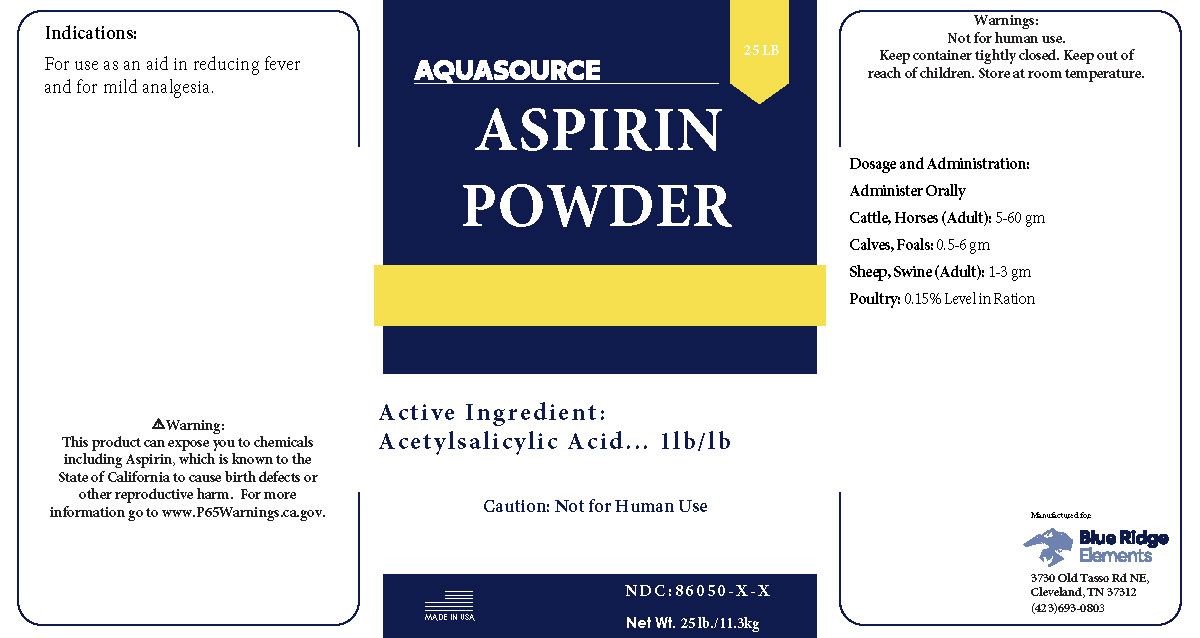 DRUG LABEL: AquaSource Aspirin Powder
NDC: 86050-1100 | Form: POWDER
Manufacturer: Blendpack, Inc.
Category: animal | Type: OTC ANIMAL DRUG LABEL
Date: 20250205

ACTIVE INGREDIENTS: ASPIRIN 1 kg/1 kg

AquaSource Aspirin Powder

Indications:

For use as an aid in reducing fever and for mild analgesia.

Warning:

This product can expose you to chemicals including Aspirin, which is known to the State of California to cause birth defects or other reproductive harm. For more information go to www.P65Warnings.ca.gov.

Warnings:

Not for human use.

Keep container tightly closed.

Keep out of reach of children.

Store at room temperature.

Dosage and Administration:

Administer Orally

Cattle, Horses (Adult): 5-60gm

Calves, Foals: 0.5-6 gm

Sheep, Swine (Adult): 1-3 gm

Poultry: 0.15% Level in Ration

PACKAGE LABEL

Add image transcription here...